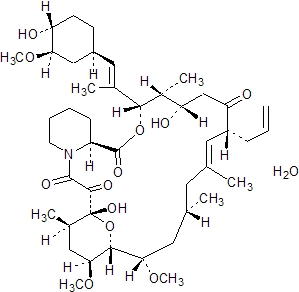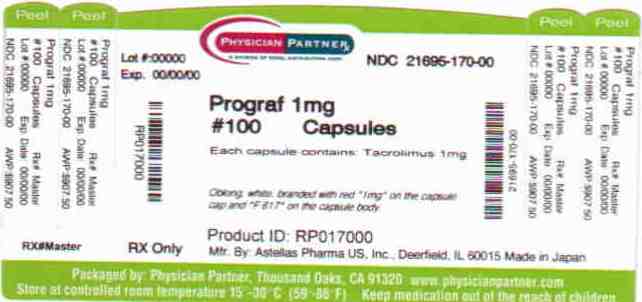 DRUG LABEL: Prograf
NDC: 21695-170 | Form: CAPSULE, GELATIN COATED
Manufacturer: Rebel Distributors Corp
Category: prescription | Type: HUMAN PRESCRIPTION DRUG LABEL
Date: 20101228

ACTIVE INGREDIENTS: anhydrous tacrolimus 1 mg/1 1
INACTIVE INGREDIENTS: CROSCARMELLOSE SODIUM; HYPROMELLOSES; magnesium stearate; LACTOSE MONOHYDRATE; gelatin; titanium dioxide

PROGRAF®
tacrolimus capsules
tacrolimus injection (for intravenous infusion only)

WARNING

Increased susceptibility to infection and the possible development of lymphoma may result from immunosuppression. Only physicians experienced in immunosuppressive therapy and management of organ transplant patients should prescribe Prograf. Patients receiving the drug should be managed in facilities equipped and staffed with adequate laboratory and supportive medical resources. The physician responsible for maintenance therapy should have complete information requisite for the follow-up of the patient.

DESCRIPTION

Prograf is available for oral administration as capsules (tacrolimus capsules) containing the equivalent of 0.5 mg, 1 mg or 5 mg of anhydrous tacrolimus. Inactive ingredients include lactose, hydroxypropyl methylcellulose, croscarmellose sodium, and magnesium stearate. The 0.5 mg capsule shell contains gelatin, titanium dioxide and ferric oxide, the 1 mg capsule shell contains gelatin and titanium dioxide, and the 5 mg capsule shell contains gelatin, titanium dioxide and ferric oxide.

Prograf is also available as a sterile solution (tacrolimus injection) containing the equivalent of 5 mg anhydrous tacrolimus in 1 mL for administration by intravenous infusion only. Each mL contains polyoxyl 60 hydrogenated castor oil (HCO-60), 200 mg, and dehydrated alcohol, USP, 80.0% v/v. Prograf injection must be diluted with 0.9% Sodium Chloride Injection or 5% Dextrose Injection before use.

Tacrolimus, previously known as FK506, is the active ingredient in Prograf. Tacrolimus is a macrolide immunosuppressant produced by Streptomyces tsukubaensis. Chemically, tacrolimus is designated as [3S-[3R*[E(1S*,3S*,4S*)], 4S*,5R*,8S*,9E,12R*,14R*,15S*,16R*,18S*,19S*,26aR*]] -5,6,8,11,12,13,14,15,16,17,18,19,24,25,26,26a-hexadecahydro-5,19-dihydroxy-3-[2-(4-hydroxy-3-methoxycyclohexyl)-1-methylethenyl]-14,16-dimethoxy-4,10,12,18-tetramethyl-8-(2-propenyl)-15,19-epoxy-3H-pyrido[2,1-c][1,4] oxaazacyclotricosine-1,7,20,21(4H,23H)-tetrone, monohydrate.

The chemical structure of tacrolimus is:

Tacrolimus has an empirical formula of C44H69NO12•H2O and a formula weight of 822.03. Tacrolimus appears as white crystals or crystalline powder. It is practically insoluble in water, freely soluble in ethanol, and very soluble in methanol and chloroform.

CLINICAL PHARMACOLOGY

Mechanism of Action

Tacrolimus prolongs the survival of the host and transplanted graft in animal transplant models of liver, kidney, heart, bone marrow, small bowel and pancreas, lung and trachea, skin, cornea, and limb.

In animals, tacrolimus has been demonstrated to suppress some humoral immunity and, to a greater extent, cell-mediated reactions such as allograft rejection, delayed type hypersensitivity, collagen-induced arthritis, experimental allergic encephalomyelitis, and graft versus host disease.

Tacrolimus inhibits T-lymphocyte activation, although the exact mechanism of action is not known. Experimental evidence suggests that tacrolimus binds to an intracellular protein, FKBP-12. A complex of tacrolimus-FKBP-12, calcium, calmodulin, and calcineurin is then formed and the phosphatase activity of calcineurin inhibited. This effect may prevent the dephosphorylation and translocation of nuclear factor of activated T-cells (NF-AT), a nuclear component thought to initiate gene transcription for the formation of lymphokines (such as interleukin-2, gamma interferon). The net result is the inhibition of T-lymphocyte activation (i.e., immunosuppression).

Pharmacokinetics

Tacrolimus activity is primarily due to the parent drug. The pharmacokinetic parameters (mean±S.D.) of tacrolimus have been determined following intravenous (IV) and/or oral (PO) administration in healthy volunteers, and in kidney transplant, liver transplant, and heart transplant patients. (See table below.)

Population | N | Route; (Dose) | Parameters
Population | N | Route; (Dose) | Cmax; (ng/mL) | Tmax; (hr) | AUC; (ng•hr/mL) | t1/2; (hr) | CI; (L/hr/kg) | V; (L/kg)
Healthy; Volunteers | 8 | IV; (0.025 mg/kg/4hr) | [not applicable] |  | 598 [AUC0-120;]; ± 125 | 34.2; ± 7.7 | 0.040; ± 0.009 | 1.91; ± 0.31
Healthy; Volunteers | 16 | PO; (5 mg) | 29.7; ± 7.2 | 1.6; ± 0.7 | 243 [AUC0-72]; ± 73 | 34.8; ± 11.4 | 0.041 [Corrected for individual bioavailability]; ± 0.008 | 1.94; ± 0.53
Kidney; Transplant; Pts | 26 | IV; (0.02 mg/kg/12 hr) |  |  | 294 [AUC0-inf;]; ± 262 | 18.8; ± 16.7 | 0.083; ± 0.050 | 1.41; ± 0.66
Kidney; Transplant; Pts | 26 | PO; (0.2 mg/kg/day) | 19.2; ± 10.3 | 3.0 | 203; ± 42 | [not available]
Kidney; Transplant; Pts | 26 | PO; (0.3 mg/kg/day) | 24.2; ± 15.8 | 1.5 | 288; ± 93
Liver; Transplant; Pts | 17 | IV; (0.05 mg/kg/12 hr) |  |  | 3300; ± 2130 | 11.7; ± 3.9 | 0.053; ± 0.017 | 0.85; ± 0.30
Liver; Transplant; Pts | 17 | PO; (0.3 mg/kg/day) | 68.5; ± 30.0 | 2.3; ± 1.5 | 519; ± 179
Heart; Transplant Patients | 11 | IV; (0.01 mg/kg/day as a continuous infusion) |  |  | 954 [AUC0-t;]; ±334 | 23.6; ±9.22 | 0.051; ±0.015
Heart; Transplant Patients | 11 | PO; (0.075mg/kg/day) [Determined after the first dose] | 14.7+7.79 | 2.1 [0.5-6.0] [Median [range]] | 82.7 [AUC0-12]; ±63.2
Heart; Transplant Patients | 14 | PO; (0.15mg/kg/day) | 24.5± 13.7 | 1.5 [0.4-4.0] | 142±116

Due to intersubject variability in tacrolimus pharmacokinetics, individualization of dosing regimen is necessary for optimal therapy. (See DOSAGE AND ADMINISTRATION). Pharmacokinetic data indicate that whole blood concentrations rather than plasma concentrations serve as the more appropriate sampling compartment to describe tacrolimus pharmacokinetics.

Absorption

Absorption of tacrolimus from the gastrointestinal tract after oral administration is incomplete and variable. The absolute bioavailability of tacrolimus was 17±10% in adult kidney transplant patients (N=26), 22±6% in adult liver transplant patients (N=17), 23±9% in adult heart transplant patients (N=11) and 18±5% in healthy volunteers (N=16).

A single dose study conducted in 32 healthy volunteers established the bioequivalence of the 1 mg and 5 mg capsules. Another single dose study in 32 healthy volunteers established the bioequivalence of the 0.5 mg and 1 mg capsules. Tacrolimus maximum blood concentrations (Cmax) and area under the curve (AUC) appeared to increase in a dose-proportional fashion in 18 fasted healthy volunteers receiving a single oral dose of 3, 7, and 10 mg.

In 18 kidney transplant patients, tacrolimus trough concentrations from 3 to 30 ng/mL measured at 10-12 hours post-dose (Cmin) correlated well with the AUC (correlation coefficient 0.93). In 24 liver transplant patients over a concentration range of 10 to 60 ng/mL, the correlation coefficient was 0.94. In 25 heart transplant patients over a concentration range of 2 to 24 ng/mL, the correlation coefficient was 0.89 after an oral dose of 0.075 or 0.15 mg/kg/day at steady-state.

Food Effects

The rate and extent of tacrolimus absorption were greatest under fasted conditions. The presence and composition of food decreased both the rate and extent of tacrolimus absorption when administered to 15 healthy volunteers.

The effect was most pronounced with a high-fat meal (848 kcal, 46% fat): mean AUC and Cmax were decreased 37% and 77%, respectively; Tmax was lengthened 5-fold. A high-carbohydrate meal (668 kcal, 85% carbohydrate) decreased mean AUC and mean Cmax by 28% and 65%, respectively.

In healthy volunteers (N=16), the time of the meal also affected tacrolimus bioavailability. When given immediately following the meal, mean Cmax was reduced 71%, and mean AUC was reduced 39%, relative to the fasted condition. When administered 1.5 hours following the meal, mean Cmax was reduced 63%, and mean AUC was reduced 39%, relative to the fasted condition.

In 11 liver transplant patients, Prograf administered 15 minutes after a high fat (400 kcal, 34% fat) breakfast, resulted in decreased AUC (27±18%) and Cmax (50±19%), as compared to a fasted state.

Distribution

The plasma protein binding of tacrolimus is approximately 99% and is independent of concentration over a range of 5-50 ng/mL. Tacrolimus is bound mainly to albumin and alpha-1-acid glycoprotein, and has a high level of association with erythrocytes. The distribution of tacrolimus between whole blood and plasma depends on several factors, such as hematocrit, temperature at the time of plasma separation, drug concentration, and plasma protein concentration. In a U.S. study, the ratio of whole blood concentration to plasma concentration averaged 35 (range 12 to 67).

Metabolism

Tacrolimus is extensively metabolized by the mixed-function oxidase system, primarily the cytochrome P-450 system (CYP3A). A metabolic pathway leading to the formation of 8 possible metabolites has been proposed. Demethylation and hydroxylation were identified as the primary mechanisms of biotransformation in vitro. The major metabolite identified in incubations with human liver microsomes is 13-demethyl tacrolimus. In in vitro studies, a 31-demethyl metabolite has been reported to have the same activity as tacrolimus.

Excretion

The mean clearance following IV administration of tacrolimus is 0.040, 0.083, and 0.053, and 0.051 L/hr/kg in healthy volunteers, adult kidney transplant patients, adult liver transplant patients, and adult heart transplant patients, respectively. In man, less than 1% of the dose administered is excreted unchanged in urine.

In a mass balance study of IV administered radiolabeled tacrolimus to 6 healthy volunteers, the mean recovery of radiolabel was 77.8±12.7%. Fecal elimination accounted for 92.4±1.0% and the elimination half-life based on radioactivity was 48.1±15.9 hours whereas it was 43.5±11.6 hours based on tacrolimus concentrations. The mean clearance of radiolabel was 0.029±0.015 L/hr/kg and clearance of tacrolimus was 0.029±0.009 L/hr/kg. When administered PO, the mean recovery of the radiolabel was 94.9±30.7%. Fecal elimination accounted for 92.6±30.7%, urinary elimination accounted for 2.3±1.1% and the elimination half-life based on radioactivity was 31.9±10.5 hours whereas it was 48.4± 12.3 hours based on tacrolimus concentrations. The mean clearance of radiolabel was 0.226±0.116 L/hr/kg and clearance of tacrolimus 0.172± 0.088 L/hr/kg.

Special Populations

Pediatric

Pharmacokinetics of tacrolimus have been studied in liver transplantation patients, 0.7 to 13.2 years of age. Following IV administration of a 0.037 mg/kg/day dose to 12 pediatric patients, mean terminal half-life, volume of distribution and clearance were 11.5±3.8 hours, 2.6±2.1 L/kg and 0.138± 0.071 L/hr/kg, respectively. Following oral administration to 9 patients, mean AUC and Cmax were 337±167 ng·hr/mL and 48.4±27.9 ng/mL, respectively. The absolute bioavailability was 31±24%.

Whole blood trough concentrations from 31 patients less than 12 years old showed that pediatric patients needed higher doses than adults to achieve similar tacrolimus trough concentrations. (See DOSAGE AND ADMINISTRATION).

Renal and Hepatic Insufficiency

The mean pharmacokinetic parameters for tacrolimus following single administrations to patients with renal and hepatic impairment are given in the following table

Population; (No. of Patients) | Dose | AUC0-t; (ng·hr/; mL) | t1/2; (hr) | V; (L/kg) | CI; (L/hr/kg)
Renal; Impairment; (n=12) | 0.02; mg/kg/4hr; IV | 393±123; (t=60 hr) | 26.3 ±9.2 | 1.07; ±0.20 | 0.038; ±0.014
Mild Hepatic; Impairment; (n=6) | 0.02; mg/kg/4hr; IV | 367±107; (t=72 hr) | 60.6±43.8; Range: 27.8 – 141 | 3.1±1.6 | 0.042; ±0.02
Mild Hepatic; Impairment; (n=6) | 7.7 mg; PO | 488±320; (t=72 hr) | 66.1±44.8; Range: 29.5 – 138 | 3.7±4.7 [corrected for bioavailability] | 0.034; ±0.019
Severe; Hepatic; Impairment; (n=6, IV) | 0.02 mg/kg/4hr; IV (n=2); 0.01 mg/kg/8hr; IV (n=4) | 762±204; (t=120 hr); 289±117; (t=144 hr) | 198±158; Range:81-436 | 3.9±1.0 | 0.017; ±0.013
(n=5, PO) [1 patient did not receive the PO dose] | 8 mg PO; (n=1); 5 mg PO; (n=4); 4 mg PO; (n=1) | 658; (t=120 hr); 533±156 (t=144 hr) | 119±35; Range: 85-178 | 3.1±3.4 | 0.016; ±0.011

Renal Insufficiency: Tacrolimus pharmacokinetics following a single IV administration were determined in 12 patients (7 not on dialysis and 5 on dialysis, serum creatinine of 3.9±1.6 and 12.0±2.4 mg/dL, respectively) prior to their kidney transplant. The pharmacokinetic parameters obtained were similar for both groups.

The mean clearance of tacrolimus in patients with renal dysfunction was similar to that in normal volunteers (see previous table).

Hepatic Insufficiency: Tacrolimus pharmacokinetics have been determined in six patients with mild hepatic dysfunction (mean Pugh score: 6.2) following single IV and oral administrations. The mean clearance of tacrolimus in patients with mild hepatic dysfunction was not substantially different from that in normal volunteers (see previous table). Tacrolimus pharmacokinetics were studied in 6 patients with severe hepatic dysfunction (mean Pugh score: >10). The mean clearance was substantially lower in patients with severe hepatic dysfunction, irrespective of the route of administration.

Race

A formal study to evaluate the pharmacokinetic disposition of tacrolimus in Black transplant patients has not been conducted. However, a retrospective comparison of Black and Caucasian kidney transplant patients indicated that Black patients required higher tacrolimus doses to attain similar trough concentrations. (See DOSAGE AND ADMINISTRATION.)

Gender

A formal study to evaluate the effect of gender on tacrolimus pharmacokinetics has not been conducted, however, there was no difference in dosing by gender in the kidney transplant trial. A retrospective comparison of pharmacokinetics in healthy volunteers, and in kidney, liver and heart transplant patients indicated no gender-based differences.

CLINICAL STUDIES

Liver Transplantation

The safety and efficacy of Prograf-based immunosuppression following orthotopic liver transplantation were assessed in two prospective, randomized, non-blinded multicenter studies. The active control groups were treated with a cyclosporine-based immunosuppressive regimen. Both studies used concomitant adrenal corticosteroids as part of the immunosuppressive regimens. These studies were designed to evaluate whether the two regimens were therapeutically equivalent, with patient and graft survival at 12 months following transplantation as the primary endpoints. The Prograf-based immunosuppressive regimen was found to be equivalent to the cyclosporine-based immunosuppressive regimens.

In one trial, 529 patients were enrolled at 12 clinical sites in the United States; prior to surgery, 263 were randomized to the Prograf-based immunosuppressive regimen and 266 to a cyclosporine-based immunosuppressive regimen (CBIR). In 10 of the 12 sites, the same CBIR protocol was used, while 2 sites used different control protocols. This trial excluded patients with renal dysfunction, fulminant hepatic failure with Stage IV encephalopathy, and cancers; pediatric patients (≤ 12 years old) were allowed.

In the second trial, 545 patients were enrolled at 8 clinical sites in Europe; prior to surgery, 270 were randomized to the Prograf-based immunosuppressive regimen and 275 to CBIR. In this study, each center used its local standard CBIR protocol in the active-control arm. This trial excluded pediatric patients, but did allow enrollment of subjects with renal dysfunction, fulminant hepatic failure in Stage IV encephalopathy, and cancers other than primary hepatic with metastases.

One-year patient survival and graft survival in the Prograf-based treatment groups were equivalent to those in the CBIR treatment groups in both studies. The overall 1-year patient survival (CBIR and Prograf-based treatment groups combined) was 88% in the U.S. study and 78% in the European study. The overall 1-year graft survival (CBIR and Prograf-based treatment groups combined) was 81% in the U.S. study and 73% in the European study. In both studies, the median time to convert from IV to oral Prograf dosing was 2 days.

Because of the nature of the study design, comparisons of differences in secondary endpoints, such as incidence of acute rejection, refractory rejection or use of OKT3 for steroid-resistant rejection, could not be reliably made.

Kidney Transplantation

Prograf/azathioprine

Prograf-based immunosuppression in conjunction with azathioprine and corticosteroids following kidney transplantation was assessed in a Phase 3 randomized, multicenter, non-blinded, prospective study. There were 412 kidney transplant patients enrolled at 19 clinical sites in the United States. Study therapy was initiated when renal function was stable as indicated by a serum creatinine ≤ 4 mg/dL (median of 4 days after transplantation, range 1 to 14 days). Patients less than 6 years of age were excluded.

There were 205 patients randomized to Prograf-based immunosuppression and 207 patients were randomized to cyclosporine-based immunosuppression. All patients received prophylactic induction therapy consisting of an antilymphocyte antibody preparation, corticosteroids and azathioprine. Overall 1 year patient and graft survival was 96.1% and 89.6%, respectively and was equivalent between treatment arms.

Because of the nature of the study design, comparisons of differences in secondary endpoints, such as incidence of acute rejection, refractory rejection or use of OKT3 for steroid-resistant rejection, could not be reliably made.

Prograf/mycophenolate mofetil (MMF)

Prograf-based immunosuppression in conjunction with MMF, corticosteroids, and induction has been studied. In a randomized, open-label, multi-center trial (Study 1), 1589 kidney transplant patients received Prograf (Group C, n=401), sirolimus (Group D, n=399), or one of two cyclosporine regimens (Group A, n=390 and Group B, n=399) in combination with MMF and corticosteroids; all patients, except those in one of the two cyclosporine groups, also received induction with daclizumab. The study was conducted outside the United States; the study population was 93% Caucasian. In this study, mortality at 12 months in patients receiving Prograf/MMF was similar (2.7%) compared to patients receiving cyclosporine/MMF (3.3% and 1.8%) or sirolimus/MMF (3.0%). Patients in the Prograf group exhibited higher estimated creatinine clearance rates (eCLcr) using the Cockcroft-Gault formula (Table 1) and experienced fewer efficacy failures, defined as biopsy proven acute rejection (BPAR), graft loss, death, and/or lost to follow-up (Table 2) in comparison to each of the other three groups. Patients randomized to Prograf/MMF were more likely to develop diarrhea and diabetes after the transplantation and experienced similar rates of infections compared to patients randomized to either cyclosporine/MMF regimen (see ADVERSE REACTIONS).

Table 1: Estimated Creatinine Clearance at 12 Months in Study 1
Group | eCLcr [mL/min] at Month 12 [All death/graft loss (n=41, 27, 23 and 42 in Groups A, B, C and D) and patients whose last recorded creatinine values were prior to month 3 visit (n=10, 9, 7 and 9 in Groups A, B, C and D) were inputed with GFR of 10 mL/min; a subject's last observed creatinine value from month 3 on was used for the remainder of subjects with missing creatinine at month 12 (n=11, 12, 15 and 19 for Groups A, B, C and D). Weight was also imputed in the calculation of estimated GFR, if missing.]
Group | N | MEAN | SD | MEDIAN | Treatment Difference with Group C (99.2% CI [Adjusted for multiple (6) pairwise comparisons using Bonferroni corrections.])
(A) CsA/MMF/CS | 390 | 56.5 | 25.8 | 56.9 | -8.6 (-13.7, -3.7)
(B) CsA/MMF/CS/Daclizumab | 399 | 58.9 | 25.6 | 60.9 | -6.2 (-11.2, -1.2)
(C) Tac/MMF/CS/Daclizumab | 401 | 65.1 | 27.4 | 66.2 | -
(D) Siro/MMF/CS/Daclizumab | 399 | 56.2 | 27.4 | 57.3 | -8.9 (-14.1, -3.9)
Total | 1589 | 59.2 | 26.8 | 60.5
Key: CsA=Cyclosporine, CS=Corticosteroids, Tac=Tacrolimus, Siro=Sirolimus

Table 2: Incidence of BPAR, Graft Loss, Death or Loss to Follow-up at 12 Months in Study 1
 | A; N=390 | B; N=399 | C; N=401 | D; N=399
Overall Failure; Components of efficacy failure; BPAR; Graft loss excluding death; Mortality; Lost to follow-up; Treatment Difference of efficacy failure compared to Group C (99.2% CI [Adjusted for multiple (6) pairwise comparisons using Bonferroni corrections.]) | 141 (36.2%); 113 (29.0%); 28 (7.2%); 13 (3.3%); 5 (1.3%); 15.8% (7.1%, 24.3%) | 126 (31.6%); 106 (26.6%); 20 (5.0%); 7 (1.8%); 7 (1.8%); 11.2% (2.7%, 19.5%) | 82 (20.4%); 60 (15.0%); 12 (3.0%); 11 (2.7%); 5 (1.3%); - | 185 (46.4%); 152 (38.1%); 30 (7.5%); 12 (3.0%); 6 (1.5%); 26.0% (17.2%, 34.7%)
Group A =CsA/MMF/CS, B =CsA/MMF/CS/Daclizumab, C=Tac/MMF/CS/Daclizumab, and D=Siro/MMF/CS/Daclizumab

The protocol-specified target tacrolimus trough concentrations (Ctrough,Tac) were 3-7 ng/mL; however, the observed median Ctroughs,Tac approximated 7 ng/mL throughout the 12 month study (Table 3).

Table 3: Tacrolimus Whole Blood Trough Concentrations (Study 1)
Time | Median (P10-P90 [Range of Ctrough, Tac that excludes lowest 10% and highest 10% of Ctrough, Tac]) tacrolimus whole blood trough concentrations; (ng/mL)
Day 30 (N=366) | 6.9 (4.4 – 11.3)
Day 90 (N=351) | 6.8 (4.1 – 10.7)
Day 180(N=355) | 6.5 (4.0 – 9.6)
Day 365 (N=346) | 6.5 (3.8 – 10.0)

The protocol-specified target cyclosporine trough concentrations (Ctrough,CsA) for Group B were 50-100 ng/mL; however, the observed median Ctroughs,CsA approximated 100 ng/mL throughout the 12 month study. The protocol-specified target Ctroughs,CsA for Group A were 150-300 ng/mL for the first 3 months and 100-200 ng/mL from month 4 to month 12; the observed median Ctroughs, CsA approximated 225 ng/mL for the first 3 months and 140 ng/mL from month 4 to month 12.

While patients in all groups started MMF at 1g BID, the MMF dose was reduced to <2 g/day in 63% of patients in the tacrolimus treatment arm by month 12 (Table 4); approximately 50% of these MMF dose reductions were due to adverse events. By comparison, the MMF dose was reduced to <2 g/day in 49% and 45% of patients in the two cyclosporine arms (Group A and Group B, respectively), by month 12 and approximately 40% of MMF dose reductions were due to adverse events.

Table 4: MMF Dose Over Time in Prograf/MMF (Group C) (Study 1)
Time period (Days) | Time-averaged MMF dose (g/day) [Percentage of patients for each time-averaged MMF dose range during various treatment periods. Two g/day of time-averaged MMF dose means that MMF dose was not reduced in those patients during the treatment periods.]
Time period (Days) | <2.0 | 2.0 | >2.0
0-30 (N=364) | 37% | 60% | 2%
0-90 (N=373) | 47% | 51% | 2%
0-180 (N=377) | 56% | 42% | 2%
0-365 (N=380) | 63% | 36% | 1%
Time-averaged MMF dose = (total MMF dose)/(duration of treatment)

In a second randomized, open-label, multi-center trial (Study 2), 424 kidney transplant patients received Prograf (n=212) or cyclosporine (n=212) in combination with MMF 1 gram BID, basiliximab induction, and corticosteroids. In this study, the rate for the combined endpoint of biopsy proven acute rejection, graft failure, death, and/or lost to follow-up at 12 months in the Prograf/MMF group was similar to the rate in the cyclosporine/MMF group. There was, however, an imbalance in mortality at 12 months in those patients receiving Prograf/MMF (4.2%) compared to those receiving cyclosporine/MMF (2.4%), including cases attributed to overimmunosuppression (Table 5).

Table 5: Incidence of BPAR, Graft Loss, Death or Loss to Follow-up at 12 Months in Study 2
 | Prograf/MMF | Cyclosporine/MMF
 | (n=212) | (n=212)
Overall Failure | 32 (15.1%) | 36 (17.0%)
Components of efficacy failure
BPAR | 16 (7.5%) | 29 (13.7%)
Graft loss excluding death | 6 (2.8%) | 4 (1.9%)
Mortality | 9 (4.2%) | 5 (2.4%)
Lost to follow-up | 4 (1.9%) | 1 (0.5%)
Treatment Difference of efficacy failure compared
to Prograf/MMF group (95% CI [95% confidence interval calculated using Fisher's Exact Test]) | - | 1.9% (-5.2%, 9.0%)

The protocol-specified target tacrolimus whole blood trough concentrations (Ctrough,Tac) in Study 2 were 7-16 ng/mL for the first three months and 5-15 ng/mL thereafter. The observed median Ctroughs,Tac approximated 10 ng/mL during the first three months and 8 ng/mL from month 4 to month 12 (Table 6).

Table 6: Tacrolimus Whole Blood Trough Concentrations (Study 2)
Time | Median (P10-P90 [Range of Ctrough,Tac that excludes lowest 10% and highest 10% of Ctrough, Tac]) tacrolimus whole blood trough concentrations; (ng/mL)
Day 30 (N=174) | 10.5 (6.3 – 16.8)
Day 60 (N=179) | 9.2 (5.9 – 15.3)
Day 120 (N=176) | 8.3 (4.6 – 13.3)
Day 180 (N=171) | 7.8 (5.5 – 13.2)
Day 365 (N=178) | 7.1 (4.2 – 12.4)

The protocol-specified target cyclosporine whole blood concentrations (Ctrough,CsA) were 125 to 400 ng/mL for the first three months, and 100 to 300 ng/mL thereafter. The observed median Ctroughs, CsA approximated 280 ng/mL during the first three months and 190 ng/mL from month 4 to month 12.

Patients in both groups started MMF at 1g BID. The MMF dose was reduced to <2 g/day by month 12 in 62% of patients in the Prograf/MMF group (Table 7) and in 47% of patients in the cyclosporine/MMF group. Approximately 63% and 55% of these MMF dose reductions were because of adverse events in the Prograf/MMF group and the cyclosporine/MMF group, respectively.

Table 7: MMF Dose Over Time in the Prograf/MMF group (Study 2)
Time period (Days) | Time-averaged MMF dose (g/day) [Percentage of patients for each time-averaged MMF dose range during various treatment periods. Two g/day of time-averaged MMF dose means that MMF dose was not reduced in those patients during the treatment periods.]
Time period (Days) | <2.0 | 2.0 | >2.0
0-30 (N=212) | 25% | 69% | 6%
0-90 (N=212) | 41% | 53% | 6%
0-180 (N=212) | 52% | 41% | 7%
0-365 (N=212) | 62% | 34% | 4%
Time-averaged MMF dose=(total MMF dose)/(duration of treatment)

Heart Transplantation

Two open-label, randomized, comparative studies evaluated the safety and efficacy of Prograf-based and cyclosporine-based immunosuppression in primary orthotopic heart transplantation. In a Phase 3 study conducted in Europe, 314 patients received a regimen of antibody induction, corticosteroids and azathioprine in combination with Prograf or cyclosporine modified for 18 months. In a 3-arm study conducted in the US, 331 patients received corticosteroids and Prograf plus sirolimus, Prograf plus mycophenolate mofetil (MMF) or cyclosporine modified plus MMF for 1 year.

In the European Phase 3 study, patient/graft survival at 18 months posttransplant was similar between treatment arms, 91.7% in the tacrolimus group and 89.2% in the cyclosporine group. In the US study, patient and graft survival at 12 months was similar with 93.5% survival in the Prograf plus MMF group and 86.1% survival in the cyclosporine modified plus MMF group. In the European study, the cyclosporine trough concentrations were above the pre-defined target range (i.e., 100-200 ng/mL) at Day 122 and beyond in 32-68% of the patients in the cyclosporine treatment arm, whereas the tacrolimus trough concentrations were within the pre-defined target range (i.e., 5-15 ng/mL) in 74-86% of the patients in the tacrolimus treatment arm.

The US study contained a third arm of a combination regimen of sirolimus, 2 mg per day, and full-dose Prograf; however, this regimen was associated with increased risk of wound healing complications, renal function impairment, and insulin-dependent post-transplant diabetes mellitus, and is not recommended (see WARNINGS).

INDICATIONS AND USAGE

Prograf is indicated for the prophylaxis of organ rejection in patients receiving allogeneic liver, kidney, or heart transplants. It is recommended that Prograf be used concomitantly with adrenal corticosteroids. Because of the risk of anaphylaxis, Prograf injection should be reserved for patients unable to take Prograf capsules orally. In heart and kidney transplant recipients, it is recommended that Prograf be used in conjunction with azathioprine or mycophenolate mofetil (MMF). The safety and efficacy of the use of Prograf with sirolimus has not been established (see CLINICAL STUDIES).

CONTRAINDICATIONS

Prograf is contraindicated in patients with a hypersensitivity to tacrolimus. Prograf injection is contraindicated in patients with a hypersensitivity to HCO-60 (polyoxyl 60 hydrogenated castor oil).

WARNINGS

(See boxed WARNING)

Post-Transplant Diabetes Mellitus

Insulin-dependent post-transplant diabetes mellitus (PTDM) was reported in 20% of Prograf-treated kidney transplant patients without pretransplant history of diabetes mellitus in the Phase III study (See Tables Below). The median time to onset of PTDM was 68 days. Insulin dependence was reversible in 15% of these PTDM patients at one year and in 50% at 2 years post transplant. Black and Hispanic kidney transplant patients were at an increased risk of development of PTDM.

Incidence of Post Transplant Diabetes Mellitus and Insulin Use at 2 Years in Kidney Transplant Recipients in the Phase III study
Status of PTDM [use of insulin for 30 or more consecutive days, with < 5 day gap, without a prior history of insulin dependent diabetes mellitus or non insulin dependent diabetes mellitus.] | Prograf | CBIR
Patients without pretransplant history of diabetes mellitus. | 151 | 151
New onset PTDM, 1st Year | 30/151 (20%) | 6/151 (4%)
Still insulin dependent at one year in those without prior history of diabetes. | 25/151 (17%) | 5/151 (3%)
New onset PTDM post 1 year | 1 | 0
Patients with PTDM at 2 years | 16/151 (11%) | 5/151 (3%)

Development of Post Transplant Diabetes Mellitus by Race and by Treatment Group during First Year Post Kidney Transplantation in the Phase III study
Patient; Race | Prograf |  | CBIR
Patient; Race | No. of Patients at Risk | Patients Who Developed PTDM [use of insulin for 30 or more consecutive days, with < 5 day gap, without a prior history of insulin dependent diabetes mellitus or non insulin dependent diabetes mellitus.] | No. of Patients At Risk | Patients Who Developed PTDM
Black | 41 | 15 (37%) | 36 | 3 (8%)
Hispanic | 17 | 5 (29%) | 18 | 1 (6%)
Caucasian | 82 | 10 (12%) | 87 | 1 (1%)
Other | 11 | 0 (0%) | 10 | 1 (10%)
Total | 151 | 30 (20%) | 151 | 6 (4%)

Insulin-dependent post-transplant diabetes mellitus was reported in 18% and 11% of Prograf-treated liver transplant patients and was reversible in 45% and 31% of these patients at 1 year post transplant, in the U.S. and European randomized studies, respectively (See Table below). Hyperglycemia was associated with the use of Prograf in 47% and 33% of liver transplant recipients in the U.S. and European randomized studies, respectively, and may require treatment (see ADVERSE REACTIONS).

Incidence of Post Transplant Diabetes Mellitus and Insulin Use at 1 Year in Liver Transplant Recipients
Status of PTDM [use of insulin for 30 or more consecutive days, with < 5 day gap, without a prior history of insulin dependent diabetes mellitus or non insulin dependent diabetes mellitus.] | US Study |  | European Study
Status of PTDM [use of insulin for 30 or more consecutive days, with < 5 day gap, without a prior history of insulin dependent diabetes mellitus or non insulin dependent diabetes mellitus.] | Prograf | CBIR | Prograf | CBIR
Patients at risk [Patients without pretransplant history of diabetes mellitus.] | 239 | 236 | 239 | 249
New Onset PTDM | 42 (18%) | 30 (13%) | 26 (11%) | 12 (5%)
Patients still on insulin at 1 year | 23 (10%) | 19 (8%) | 18 (8%) | 6 (2%)

Insulin-dependent post-transplant diabetes mellitus was reported in 13% and 22% of Prograf-treated heart transplant patients receiving mycophenolate mofetil or azathioprine and was reversible in 30% and 17% of these patients at one year post transplant, in the US and European randomized studies, respectively (See Table below). Hyperglycemia defined as two fasting plasma glucose levels ≥126 mg/dL was reported with the use of Prograf plus mycophenolate mofetil or azathioprine in 32% and 35% of heart transplant recipients in the US and European randomized studies, respectively, and may require treatment (see ADVERSE REACTIONS).

Incidence of Post Transplant Diabetes Mellitus and Insulin Use at 1 Year in Heart Transplant Recipients
Status of PTDM [use of insulin for 30 or more consecutive days without a prior history of insulin dependent diabetes mellitus or non insulin dependent diabetes mellitus.] | US Study |  |  | European Study
Status of PTDM [use of insulin for 30 or more consecutive days without a prior history of insulin dependent diabetes mellitus or non insulin dependent diabetes mellitus.] | Prograf/Sirolimus | Prograf/MMF | Cyclosporine/MMF | Prograf/AZA | Cyclosporine/AZA
Patients at risk [Patients without pretransplant history of diabetes mellitus.] | 85 | 75 | 83 | 132 | 138
New Onset PTDM | 21 (25%) | 10 (13%) | 6 (7%) | 29 (22%) | 5 (4%)
Patients still on insulin at 1 year [7-12 months for the US Study.] | 10 (12%) | 7 (9%) | 1 (1%) | 24 (18%) | 4 (3%)

Nephrotoxicity

Prograf can cause nephrotoxicity, particularly when used in high doses. Nephrotoxicity was reported in approximately 52% of kidney transplantation patients and in 40% and 36% of liver transplantation patients receiving Prograf in the U.S. and European randomized trials, respectively, and in 59% of heart transplantation patients in a European randomized trial (see ADVERSE REACTIONS). Use of Prograf with sirolimus in heart transplantation patients in a US study was associated with increased risk of renal function impairment, and is not recommended (See CLINICAL STUDIES). More overt nephrotoxicity is seen early after transplantation, characterized by increasing serum creatinine and a decrease in urine output. Patients with impaired renal function should be monitored closely as the dosage of Prograf may need to be reduced. In patients with persistent elevations of serum creatinine who are unresponsive to dosage adjustments, consideration should be given to changing to another immunosuppressive therapy. Care should be taken in using tacrolimus with other nephrotoxic drugs. In particular, to avoid excess nephrotoxicity, Prograf should not be used simultaneously with cyclosporine. Prograf or cyclosporine should be discontinued at least 24 hours prior to initiating the other. In the presence of elevated Prograf or cyclosporine concentrations, dosing with the other drug usually should be further delayed.

Hyperkalemia

Mild to severe hyperkalemia was reported in 31% of kidney transplant recipients and in 45% and 13% of liver transplant recipients treated with Prograf in the U.S. and European randomized trials, respectively, and in 8% of heart transplant recipients in a European randomized trial and may require treatment (see ADVERSE REACTIONS). Serum potassium levels should be monitored and potassium-sparing diuretics should not be used during Prograf therapy (see PRECAUTIONS).

Neurotoxicity

Prograf can cause neurotoxicity, particularly when used in high doses. Neurotoxicity, including tremor, headache, and other changes in motor function, mental status, and sensory function were reported in approximately 55% of liver transplant recipients in the two randomized studies. Tremor occurred more often in Prograf-treated kidney transplant patients (54%) and heart transplant patients (15%) compared to cyclosporine-treated patients. The incidence of other neurological events in kidney transplant and heart transplant patients was similar in the two treatment groups (see ADVERSE REACTIONS). Tremor and headache have been associated with high whole-blood concentrations of tacrolimus and may respond to dosage adjustment. Seizures have occurred in adult and pediatric patients receiving Prograf (see ADVERSE REACTIONS). Coma and delirium also have been associated with high plasma concentrations of tacrolimus.

Patients treated with tacrolimus have been reported to develop posterior reversible encephalopathy syndrome (PRES). Symptoms indicating PRES include headache, altered mental status, seizures, visual disturbances and hypertension. Diagnosis may be confirmed by radiological procedure. If PRES is suspected or diagnosed, blood pressure control should be maintained and immediate reduction of immunosuppression is advised. This syndrome is characterized by reversal of symptoms upon reduction or discontinuation of immunosuppression.

Malignancy and Lymphoproliferative Disorders

As in patients receiving other immunosuppressants, patients receiving Prograf are at increased risk of developing lymphomas and other malignancies, particularly of the skin. The risk appears to be related to the intensity and duration of immunosuppression rather than to the use of any specific agent. A lymphoproliferative disorder (LPD) related to Epstein-Barr Virus (EBV) infection has been reported in immunosuppressed organ transplant recipients. The risk of LPD appears greatest in young children who are at risk for primary EBV infection while immunosuppressed or who are switched to Prograf following long-term immunosuppression therapy. Because of the danger of oversuppression of the immune system which can increase susceptibility to infection, combination immunosuppressant therapy should be used with caution.

Latent Viral Infections

Immunosuppressed patients are at increased risk for opportunistic infections, including activation of latent viral infections. These include BK virus associated nephropathy and JC virus associated progressive multifocal leukoencephalopathy (PML) which have been observed in patients receiving tacrolimus. These infections may lead to serious, including fatal, outcomes.

Prograf in Combination with Sirolimus

The use of full-dose Prograf with sirolimus (2 mg per day) in heart transplant recipients was associated with increased risk of wound healing complications, renal function impairment, and insulin-dependent post-transplant diabetes mellitus, and is not recommended (see CLINICAL STUDIES).

Anaphylactic Reactions

A few patients receiving Prograf injection have experienced anaphylactic reactions. Although the exact cause of these reactions is not known, other drugs with castor oil derivatives in the formulation have been associated with anaphylaxis in a small percentage of patients. Because of this potential risk of anaphylaxis, Prograf injection should be reserved for patients who are unable to take Prograf capsules.

Patients receiving Prograf injection should be under continuous observation for at least the first 30 minutes following the start of the infusion and at frequent intervals thereafter. If signs or symptoms of anaphylaxis occur, the infusion should be stopped. An aqueous solution of epinephrine should be available at the bedside as well as a source of oxygen.

PRECAUTIONS

General

Hypertension is a common adverse effect of Prograf therapy (see ADVERSE REACTIONS). Mild or moderate hypertension is more frequently reported than severe hypertension. Antihypertensive therapy may be required; the control of blood pressure can be accomplished with any of the common antihypertensive agents. Since tacrolimus may cause hyperkalemia, potassium-sparing diuretics should be avoided. While calcium-channel blocking agents can be effective in treating Prograf-associated hypertension, care should be taken since interference with tacrolimus metabolism may require a dosage reduction (see Drug Interactions).

Renally and Hepatically Impaired Patients

For patients with renal insufficiency some evidence suggests that lower doses should be used (see CLINICAL PHARMACOLOGY and DOSAGE AND ADMINISTRATION).

The use of Prograf in liver transplant recipients experiencing post-transplant hepatic impairment may be associated with increased risk of developing renal insufficiency related to high whole-blood levels of tacrolimus. These patients should be monitored closely and dosage adjustments should be considered. Some evidence suggests that lower doses should be used in these patients (see DOSAGE AND ADMINISTRATION).

Myocardial Hypertrophy

Myocardial hypertrophy has been reported in association with the administration of Prograf, and is generally manifested by echocardiographically demonstrated concentric increases in left ventricular posterior wall and interventricular septum thickness. Hypertrophy has been observed in infants, children and adults. This condition appears reversible in most cases following dose reduction or discontinuance of therapy. In a group of 20 patients with pre- and post-treatment echocardiograms who showed evidence of myocardial hypertrophy, mean tacrolimus whole blood concentrations during the period prior to diagnosis of myocardial hypertrophy ranged from 11 to 53 ng/mL in infants (N=10, age 0.4 to 2 years), 4 to 46 ng/mL in children (N=7, age 2 to 15 years) and 11 to 24 ng/mL in adults (N=3, age 37 to 53 years).

In patients who develop renal failure or clinical manifestations of ventricular dysfunction while receiving Prograf therapy, echocardiographic evaluation should be considered. If myocardial hypertrophy is diagnosed, dosage reduction or discontinuation of Prograf should be considered.

Information for Patients

Patients should be informed of the need for repeated appropriate laboratory tests while they are receiving Prograf. They should be given complete dosage instructions, advised of the potential risks during pregnancy, and informed of the increased risk of neoplasia. Patients should be informed that changes in dosage should not be undertaken without first consulting their physician.

Patients should be informed that Prograf can cause diabetes mellitus and should be advised of the need to see their physician if they develop frequent urination, increased thirst or hunger.

As with other immunosuppressive agents, owing to the potential risk of malignant skin changes, exposure to sunlight and ultraviolet (UV) light should be limited by wearing protective clothing and using a sunscreen with a high protection factor.

Laboratory Tests

Serum creatinine, potassium, and fasting glucose should be assessed regularly. Routine monitoring of metabolic and hematologic systems should be performed as clinically warranted.

Drug Interactions

Due to the potential for additive or synergistic impairment of renal function, care should be taken when administering Prograf with drugs that may be associated with renal dysfunction. These include, but are not limited to, aminoglycosides, amphotericin B, and cisplatin. Initial clinical experience with the co-administration of Prograf and cyclosporine resulted in additive/synergistic nephrotoxicity. Patients switched from cyclosporine to Prograf should receive the first Prograf dose no sooner than 24 hours after the last cyclosporine dose. Dosing may be further delayed in the presence of elevated cyclosporine levels.

Drugs that May Alter Tacrolimus Concentrations

Since tacrolimus is metabolized mainly by the CYP3A enzyme systems, substances known to inhibit these enzymes may decrease the metabolism or increase bioavailability of tacrolimus as indicated by increased whole blood or plasma concentrations. Drugs known to induce these enzyme systems may result in an increased metabolism of tacrolimus or decreased bioavailability as indicated by decreased whole blood or plasma concentrations. Monitoring of blood concentrations and appropriate dosage adjustments are essential when such drugs are used concomitantly.

[This table is not all inclusive.] Drugs That May Increase Tacrolimus Blood Concentrations
Calcium; Channel Blockers | Antifungal; Agents | Macrolide; Antibiotics
diltiazem | clotrimazole | clarithromycin
nicardipine | fluconazole | erythromycin
nifedipine | itraconazole | troleandomycin
verapamil | ketoconazole [In a study of 6 normal volunteers, a significant increase in tacrolimus oral bioavailability (14±5% vs. 30±8%) was observed with concomitant ketoconazole administration (200 mg). The apparent oral clearance of tacrolimus during ketoconazole administration was significantly decreased compared to tacrolimus alone (0.430±0.129 L/hr/kg vs. 0.148±0.043 L/hr/kg). Overall, IV clearance of tacrolimus was not significantly changed by ketoconazole co-administration, although it was highly variable between patients.]
 | voriconazole
Gastrointestinal Prokinetic Agents | Other; Drugs
cisapride | bromocriptine
metoclopramide | chloramphenicol
 | cimetidine
 | cyclosporine
 | danazol
 | ethinyl estradiol
 | methylprednisolone
 | lansoprazole [Lansoprazole (CYP2C19, CYP3A4 substrate) may potentially inhibit CYP3A4-mediated metabolism of tacrolimus and thereby substantially increase tacrolimus whole blood concentrations, especially in transplant patients who are intermediate or poor CYP2C19 metabolizers, as compared to those patients who are efficient CYP2C19 metabolizers.]
 | omeprazole
 | protease inhibitors
 | nefazodone
 | magnesium-aluminum-hydroxide

[This table is not all inclusive.] Drugs That May Decrease Tacrolimus Blood Concentrations
Anticonvulsants | Antimicrobials
carbamazepine | rifabutin
phenobarbital | caspofungin
phenytoin | rifampin
Herbal Preparations | Other Drugs
St. John’s Wort | sirolimus

St. John’s Wort (Hypericum perforatum) induces CYP3A4 and P-glycoprotein. Since tacrolimus is a substrate for CYP3A4, there is the potential that the use of St. John’s Wort in patients receiving Prograf could result in reduced tacrolimus levels.

In a single-dose crossover study in healthy volunteers, co-administration of tacrolimus and magnesium-aluminum-hydroxide resulted in a 21% increase in the mean tacrolimus AUC and a 10% decrease in the mean tacrolimus Cmax relative to tacrolimus administration alone.

In a study of 6 normal volunteers, a significant decrease in tacrolimus oral bioavailability (14±6% vs. 7±3%) was observed with concomitant rifampin administration (600 mg). In addition, there was a significant increase in tacrolimus clearance (0.036±0.008 L/hr/kg vs. 0.053±0.010 L/hr/kg) with concomitant rifampin administration.

Interaction studies with drugs used in HIV therapy have not been conducted. However, care should be exercised when drugs that are nephrotoxic (e.g., ganciclovir) or that are metabolized by CYP3A (e.g., nelfinavir, ritonavir) are administered concomitantly with tacrolimus. Based on a clinical study of 5 liver transplant recipients, co-administration of tacrolimus with nelfinavir increased blood concentrations of tacrolimus significantly and, as a result, a reduction in the tacrolimus dose by an average of 16-fold was needed to maintain mean trough tacrolimus blood concentrations of 9.7 ng/mL. Thus, frequent monitoring of tacrolimus blood concentrations and appropriate dosage adjustments are essential when nelfinavir is used concomitantly. Tacrolimus may affect the pharmacokinetics of other drugs (e.g., phenytoin) and increase their concentration. Grapefruit juice affects CYP3A-mediated metabolism and should be avoided (see DOSAGE AND ADMINISTRATION).

Following co-administration of tacrolimus and sirolimus (2 or 5 mg/day) in stable renal transplant patients, mean tacrolimus AUC0-12 and Cmin decreased approximately by 30% relative to tacrolimus alone. Mean tacrolimus AUC0-12 and Cmin following co-administration of 1 mg/day of sirolimus decreased approximately 3% and 11%, respectively. The safety and efficacy of tacrolimus used in combination with sirolimus for the prevention of graft rejection has not been established and is not recommended.

Other Drug Interactions

Immunosuppressants may affect vaccination. Therefore, during treatment with Prograf, vaccination may be less effective. The use of live vaccines should be avoided; live vaccines may include, but are not limited to measles, mumps, rubella, oral polio, BCG, yellow fever, and TY 21a typhoid.^1

At a given MMF dose, mycophenolic acid (MPA) exposure is higher with Prograf co-administration than with cyclosporine co-administration due to the differences in the interruption of the enterohepatic recirculation of MPA. Clinicians should be aware that there is also a potential for increased MPA exposure after crossover from cyclosporine to tacrolimus in patients concomitantly receiving MMF or MPA.

Carcinogenesis, Mutagenesis and Impairment of Fertility

An increased incidence of malignancy is a recognized complication of immunosuppression in recipients of organ transplants. The most common forms of neoplasms are non-Hodgkin’s lymphomas and carcinomas of the skin. As with other immunosuppressive therapies, the risk of malignancies in Prograf recipients may be higher than in the normal, healthy population. Lymphoproliferative disorders associated with Epstein-Barr Virus infection have been seen. It has been reported that reduction or discontinuation of immunosuppression may cause the lesions to regress.

No evidence of genotoxicity was seen in bacterial (Salmonella and E. coli) or mammalian (Chinese hamster lung-derived cells) in vitro assays of mutagenicity, the in vitro CHO/HGPRT assay of mutagenicity, or in vivo clastogenicity assays performed in mice; tacrolimus did not cause unscheduled DNA synthesis in rodent hepatocytes.

Carcinogenicity studies were carried out in male and female rats and mice. In the 80-week mouse study and in the 104-week rat study no relationship of tumor incidence to tacrolimus dosage was found. The highest doses used in the mouse and rat studies were 0.8 – 2.5 times (mice) and 3.5 – 7.1 times (rats) the recommended clinical dose range of 0.1 – 0.2 mg/kg/day when corrected for body surface area.

No impairment of fertility was demonstrated in studies of male and female rats. Tacrolimus, given orally at 1.0 mg/kg (0.7 – 1.4X the recommended clinical dose range of 0.1 – 0.2 mg/kg/day based on body surface area corrections) to male and female rats, prior to and during mating, as well as to dams during gestation and lactation, was associated with embryolethality and with adverse effects on female reproduction. Effects on female reproductive function (parturition) and embryolethal effects were indicated by a higher rate of pre-implantation loss and increased numbers of undelivered and nonviable pups. When given at 3.2 mg/kg (2.3 – 4.6X the recommended clinical dose range based on body surface area correction), tacrolimus was associated with maternal and paternal toxicity as well as reproductive toxicity including marked adverse effects on estrus cycles, parturition, pup viability, and pup malformations.

Pregnancy: Category C

In reproduction studies in rats and rabbits, adverse effects on the fetus were observed mainly at dose levels that were toxic to dams. Tacrolimus at oral doses of 0.32 and 1.0 mg/kg during organogenesis in rabbits was associated with maternal toxicity as well as an increase in incidence of abortions; these doses are equivalent to 0.5 – 1X and 1.6 – 3.3X the recommended clinical dose range (0.1 – 0.2 mg/kg) based on body surface area corrections. At the higher dose only, an increased incidence of malformations and developmental variations was also seen. Tacrolimus, at oral doses of 3.2 mg/kg during organogenesis in rats, was associated with maternal toxicity and caused an increase in late resorptions, decreased numbers of live births, and decreased pup weight and viability. Tacrolimus, given orally at 1.0 and 3.2 mg/kg (equivalent to 0.7 – 1.4X and 2.3 – 4.6X the recommended clinical dose range based on body surface area corrections) to pregnant rats after organogenesis and during lactation, was associated with reduced pup weights.

No reduction in male or female fertility was evident.

There are no adequate and well-controlled studies in pregnant women. Tacrolimus is transferred across the placenta. The use of tacrolimus during pregnancy has been associated with neonatal hyperkalemia and renal dysfunction. Prograf should be used during pregnancy only if the potential benefit to the mother justifies potential risk to the fetus.

Nursing Mothers

Since tacrolimus is excreted in human milk, nursing should be avoided.

Pediatric Patients

Experience with Prograf in pediatric kidney and heart transplant patients is limited. Successful liver transplants have been performed in pediatric patients (ages up to 16 years) using Prograf. Two randomized active-controlled trials of Prograf in primary liver transplantation included 56 pediatric patients. Thirty-one patients were randomized to Prograf-based and 25 to cyclosporine-based therapies. Additionally, a minimum of 122 pediatric patients were studied in an uncontrolled trial of tacrolimus in living related donor liver transplantation. Pediatric patients generally required higher doses of Prograf to maintain blood trough concentrations of tacrolimus similar to adult patients (see DOSAGE AND ADMINISTRATION).

ADVERSE REACTIONS

Liver Transplantation

The principal adverse reactions of Prograf are tremor, headache, diarrhea, hypertension, nausea, and abnormal renal function. These occur with oral and IV administration of Prograf and may respond to a reduction in dosing. Diarrhea was sometimes associated with other gastrointestinal complaints such as nausea and vomiting.

Hyperkalemia and hypomagnesemia have occurred in patients receiving Prograf therapy. Hyperglycemia has been noted in many patients; some may require insulin therapy (see WARNINGS).

The incidence of adverse events was determined in two randomized comparative liver transplant trials among 514 patients receiving tacrolimus and steroids and 515 patients receiving a cyclosporine-based regimen (CBIR). The proportion of patients reporting more than one adverse event was 99.8% in the tacrolimus group and 99.6% in the CBIR group. Precautions must be taken when comparing the incidence of adverse events in the U.S. study to that in the European study. The 12-month posttransplant information from the U.S. study and from the European study is presented below. The two studies also included different patient populations and patients were treated with immunosuppressive regimens of differing intensities. Adverse events reported in ≥ 15% in tacrolimus patients (combined study results) are presented below for the two controlled trials in liver transplantation:

LIVER TRANSPLANTATION: ADVERSE EVENTS OCCURRING IN ≥ 15% OF PROGRAF-TREATED PATIENTS
 | U.S. STUDY |  | EUROPEAN STUDY
 | Prograf; (N=250) | CBIR; (N=250) | Prograf; (N=264) | CBIR; (N=265)
Nervous System
Headache (see WARNINGS); Tremor (see WARNINGS); Insomnia; Paresthesia | 64%; 56%; 64%; 40% | 60%; 46%; 68%; 30% | 37%; 48%; 32%; 17% | 26%; 32%; 23%; 17%
Gastrointestinal
Diarrhea; Nausea; Constipation; LFT Abnormal; Anorexia; Vomiting | 72%; 46%; 24%; 36%; 34%; 27% | 47%; 37%; 27%; 30%; 24%; 15% | 37%; 32%; 23%; 6%; 7%; 14% | 27%; 27%; 21%; 5%; 5%; 11%
Cardiovascular
Hypertension (see PRECAUTIONS) | 47% | 56% | 38% | 43%
Urogenital
Kidney Function Abnormal (see WARNINGS); Creatinine Increased (see WARNINGS); BUN Increased (see WARNINGS); Urinary Tract Infection; Oliguria | 40%; 39%; 30%; 16%; 18% | 27%; 25%; 22%; 18%; 15% | 36%; 24%; 12%; 21%; 19% | 23%; 19%; 9%; 19%; 12%
Metabolic and Nutritional
Hyperkalemia (see WARNINGS); Hypokalemia; Hyperglycemia (see WARNINGS); Hypomagnesemia | 45%; 29%; 47%; 48% | 26%; 34%; 38%; 45% | 13%; 13%; 33%; 16% | 9%; 16%; 22%; 9%
Hemic and Lymphatic
Anemia; Leukocytosis; Thrombocytopenia | 47%; 32%; 24% | 38%; 26%; 20% | 5%; 8%; 14% | 1%; 8%; 19%
Miscellaneous
Abdominal Pain; Pain; Fever; Asthenia; Back Pain; Ascites; Peripheral Edema | 59%; 63%; 48%; 52%; 30%; 27%; 26% | 54%; 57%; 56%; 48%; 29%; 22%; 26% | 29%; 24%; 19%; 11%; 17%; 7%; 12% | 22%; 22%; 22%; 7%; 17%; 8%; 14%
Respiratory System
Pleural Effusion; Atelectasis; Dyspnea | 30%; 28%; 29% | 32%; 30%; 23% | 36%; 5%; 5% | 35%; 4%; 4%
Skin and Appendages
Pruritus; Rash | 36%; 24% | 20%; 19% | 15%; 10% | 7%; 4%

Less frequently observed adverse reactions in both liver transplantation and kidney transplantation patients are described under the subsection Less Frequently Reported Adverse Reactions below.

Kidney Transplantation

The most common adverse reactions reported were infection, tremor, hypertension, abnormal renal function, constipation, diarrhea, headache, abdominal pain and insomnia.

Adverse events that occurred in ≥ 15% of kidney transplant patients treated with Prograf in conjunction with azathioprine are presented below:

KIDNEY TRANSPLANTATION: ADVERSE EVENTS OCCURRING IN ≥ 15% OF PATIENTS TREATED WITH PROGRAF IN CONJUNCTION WITH AZATHIOPRINE
 | Prograf; (N=205) | CBIR; (N=207)
Nervous System
Tremor (see WARNINGS); Headache (see WARNINGS); Insomnia; Paresthesia; Dizziness | 54%; 44%; 32%; 23%; 19% | 34%; 38%; 30%; 16%; 16%
Gastrointestinal
Diarrhea; Nausea; Constipation; Vomiting; Dyspepsia | 44%; 38%; 35%; 29%; 28% | 41%; 36%; 43%; 23%; 20%
Cardiovascular
Hypertension (see PRECAUTIONS); Chest pain | 50%; 19% | 52%; 13%
Urogenital
Creatinine Increased (see WARNINGS); Urinary Tract Infection | 45%; 34% | 42%; 35%
Metabolic and Nutritional
Hypophosphatemia; Hypomagnesemia; Hyperlipemia; Hyperkalemia (see WARNINGS); Diabetes Mellitus (see WARNINGS); Hypokalemia; Hyperglycemia (see WARNINGS); Edema | 49%; 34%; 31%; 31%; 24%; 22%; 22%; 18% | 53%; 17%; 38%; 32%; 9%; 25%; 16%; 19%
Hemic and Lymphatic
Anemia; Leukopenia | 30%; 15% | 24%; 17%
Miscellaneous
Infection; Peripheral Edema; Asthenia; Abdominal Pain; Pain; Fever; Back Pain | 45%; 36%; 34%; 33%; 32%; 29%; 24% | 49%; 48%; 30%; 31%; 30%; 29%; 20%
Respiratory System
Dyspnea; Cough Increased | 22%; 18% | 18%; 15%
Musculoskeletal
Arthralgia | 25% | 24%
Skin
Rash; Pruritus | 17%; 15% | 12%; 7%

Adverse events that occurred in ≥ 10% of kidney transplant patients treated with Prograf in conjunction with MMF in Study 1* are presented below:

KIDNEY TRANSPLANTATION: ADVERSE EVENTS OCCURRING IN ≥ 10% OF PROGRAF-TREATED PATIENTS
 | Prograf (Group C) | Cyclosporine (Group A) | Cyclosporine (Group B)
 | (N=403) | (N=384) | (N=408)
Anemia | 17% | 19% | 17%
Leucopenia | 13% | 10% | 10%
Diarrhea | 25% | 16% | 13%
Edema peripheral | 11% | 12% | 13%
Urinary tract infection | 24% | 28% | 24%
Hyperlipidemia | 10% | 15% | 13%
Hypertension (see PRECAUTIONS) | 13% | 14% | 12%
*Study 1 was conducted entirely outside of the United States. Such studies often report a lower incidence of adverse events in comparison to US studies.

Adverse events that occurred in ≥15% of kidney transplant patients treated with Prograf in conjunction with MMF in Study 2 are presented below:

KIDNEY TRANSPLANTATION: ADVERSE EVENTS OCCURRING IN ≥ 15% OF PROGRAF-TREATED PATIENTS
 | Prograf | Cyclosporine
 | (N=212) | (N=212)
Gastrointestinal Disorders
Diarrhea | 44% | 26%
Nausea | 39% | 47%
Constipation | 36% | 41%
Vomiting | 26% | 25%
Dyspepsia | 18% | 15%
Injury, Poisoning, and Procedural Complications
Post Procedural Pain | 29% | 27%
Incision Site Complication | 28% | 23%
Graft Dysfunction | 24% | 18%
Metabolism and Nutrition Disorders
Hypomagnesemia | 28% | 22%
Hypophosphatemia | 28% | 21%
Hyperkalemia (see WARNINGS) | 26% | 19%
Hyperglycemia (see WARNINGS) | 21% | 15%
Hyperlipidemia | 18% | 25%
Hypokalemia | 16% | 18%
Nervous System Disorders
Tremor | 34% | 20%
Headache | 24% | 25%
Blood and Lymphatic System Disorders
Anemia | 30% | 28%
Leukopenia | 16% | 12%
Miscellaneous
Edema Peripheral | 35% | 46%
Hypertension (see PRECAUTIONS) | 32% | 35%
Insomnia | 30% | 21%
Urinary Tract Infection | 26% | 22%
Blood creatinine increased | 23% | 23%

Less frequently observed adverse reactions in both liver transplantation and kidney transplantation patients are described under the subsection Less Frequently Reported Adverse Reactions shown below.

Heart Transplantation

The more common adverse reactions in Prograf-treated heart transplant recipients were abnormal renal function , hypertension, diabetes mellitus, CMV infection, tremor, hyperglycemia, leukopenia, infection, and hyperlipemia.

Adverse events in heart transplant patients in the European trial are presented below:

HEART TRANSPLANTATION: ADVERSE EVENTS OCCURRING IN ≥ 15% OF PROGRAF-TREATED PATIENTS
COSTART Body System; COSTART Term | Prograf+; Azathioprine; (n=157) | CsA + Azathioprine; (n=157)
Cardiovascular System
Hypertension (See PRECAUTIONS) | 62% | 69%
Pericardial effusion | 15% | 14%
Body as a Whole
CMV infection | 32% | 30%
Infection | 24% | 21%
Metabolic and Nutritional Disorders
Hyperlipemia | 18% | 27%
Diabetes Mellitus (See WARNINGS) | 26% | 16%
Hyperglycemia (See WARNINGS) | 23% | 17%
Hemic and Lymphatic System
Leukopenia | 48% | 39%
Anemia | 50% | 36%
Urogenital System
Kidney function abnormal (See WARNINGS) | 56% | 57%
Urinary tract infection | 16% | 12%
Respiratory System
Bronchitis | 17% | 18%
Nervous System
Tremor (See WARNINGS) | 15% | 6%

In the European study, the cyclosporine trough concentrations were above the pre-defined target range (i.e., 100-200 ng/mL) at Day 122 and beyond in 32-68% of the patients in the cyclosporine treatment arm, whereas the tacrolimus trough concentrations were within the pre-defined target range (i.e., 5-15 ng/mL) in 74-86% of the patients in the tacrolimus treatment arm.

Only selected targeted treatment-emergent adverse events were collected in the US heart transplantation study. Those events that were reported at a rate of 15% or greater in patients treated with Prograf and mycophenolate mofetil include the following: any target adverse events (99.1%), hypertension (88.8%), hyperglycemia requiring antihyperglycemic therapy (70.1%) (see WARNINGS), hypertriglyceridemia (65.4%), anemia (hemoglobin <10.0 g/dL) (65.4%), fasting blood glucose >140 mg/dL (on two separate occasions) (60.7%) (see WARNINGS), hypercholesterolemia (57.0%), hyperlipidemia (33.6%), WBCs <3000 cells/mcL (33.6%), serious bacterial infections (29.9%), magnesium <1.2 mEq/L (24.3%), platelet count <75,000 cells/mcL (18.7%), and other opportunistic infections (15.0%).

Other targeted treatment-emergent adverse events in Prograf-treated patients occurred at a rate of less than 15%, and include the following: Cushingoid features, impaired wound healing, hyperkalemia, Candida infection, and CMV infection/syndrome.

Less Frequently Reported Adverse Reactions

The following adverse events were reported in either liver, kidney, and/or heart transplant recipients who were treated with tacrolimus in clinical trials.

Nervous System

(see WARNINGS)

Abnormal dreams, agitation, amnesia, anxiety, confusion, convulsion, crying, depression, dizziness, elevated mood, emotional lability, encephalopathy, haemorrhagic stroke, hallucinations, headache, hypertonia, incoordination, insomnia, monoparesis, myoclonus, nerve compression, nervousness, neuralgia, neuropathy, paresthesia, paralysis flaccid, psychomotor skills impaired, psychosis, quadriparesis, somnolence, thinking abnormal, vertigo, writing impaired

Special Senses

Abnormal vision, amblyopia, ear pain, otitis media, tinnitus

Gastrointestinal

Anorexia, cholangitis, cholestatic jaundice, diarrhea, duodenitis, dyspepsia, dysphagia, esophagitis, flatulence, gastritis, gastroesophagitis, gastrointestinal hemorrhage, GGT increase, GI disorder, GI perforation, hepatitis, hepatitis granulomatous, ileus, increased appetite, jaundice, liver damage, liver function test abnormal, nausea, nausea and vomiting, oesophagitis ulcerative, oral moniliasis, pancreatic pseudocyst, rectal disorder, stomatitis, vomiting

Cardiovascular

Abnormal ECG, angina pectoris, arrhythmia, atrial fibrillation, atrial flutter, bradycardia, cardiac fibrillation, cardiopulmonary failure, cardiovascular disorder, chest pain, congestive heart failure, deep thrombophlebitis, echocardiogram abnormal, electrocardiogram QRS complex abnormal, electrocardiogram ST segment abnormal, heart failure, heart rate decreased, hemorrhage, hypotension, peripheral vascular disorder, phlebitis, postural hypotension, syncope, tachycardia, thrombosis, vasodilatation

Urogenital

(see WARNINGS)

Acute kidney failure, albuminuria, BK nephropathy, bladder spasm, cystitis, dysuria, hematuria, hydronephrosis, kidney failure, kidney tubular necrosis, nocturia, oliguria, pyuria, toxic nephropathy, urge incontinence, urinary frequency, urinary incontinence, urinary retention, vaginitis

Metabolic/Nutritional

Acidosis, alkaline phosphatase increased, alkalosis, ALT (SGPT) increased, AST (SGOT) increased, bicarbonate decreased, bilirubinemia, BUN increased, dehydration, edema, GGT increased, gout, healing abnormal, hypercalcemia, hypercholesterolemia, hyperkalemia, hyperlipemia, hyperphosphatemia, hyperuricemia, hypervolemia, hypocalcemia, hypoglycemia, hypokalemia, hypomagnesemia, hyponatremia, hypophosphatemia, hypoproteinemia, lactic dehydrogenase increase, peripheral edema, weight gain

Endocrine

(see PRECAUTIONS)

Cushing’s syndrome, diabetes mellitus

Hemic/Lymphatic

Coagulation disorder, ecchymosis, haematocrit increased, haemoglobin abnormal, hypochromic anemia, leukocytosis, leukopenia, polycythemia, prothrombin decreased, serum iron decreased, thrombocytopenia

Miscellaneous

Abdomen enlarged, abdominal pain, abscess, accidental injury, allergic reaction, asthenia, back pain, cellulitis, chills, fall, feeling abnormal, fever, flu syndrome, generalized edema, hernia, mobility decreased, pain, peritonitis, photosensitivity reaction, sepsis, temperature intolerance, ulcer

Musculoskeletal

Arthralgia, cramps, generalized spasm, joint disorder, leg cramps, myalgia, myasthenia, osteoporosis

Respiratory

Asthma, bronchitis, cough increased, dyspnea, emphysema, hiccups, lung disorder, lung function decreased, pharyngitis, pleural effusion, pneumonia, pneumothorax, pulmonary edema, respiratory disorder, rhinitis, sinusitis, voice alteration

Skin

Acne, alopecia, exfoliative dermatitis, fungal dermatitis, herpes simplex, herpes zoster, hirsutism, neoplasm skin benign, skin discoloration, skin disorder, skin ulcer, sweating.

Post Marketing Adverse Events

The following adverse events have been reported from worldwide marketing experience with Prograf. Because these events are reported voluntarily from a population of uncertain size, are associated with concomitant diseases and multiple drug therapies and surgical procedures, it is not always possible to reliably estimate their frequency or establish a causal relationship to drug exposure. Decisions to include these events in labeling are typically based on one or more of the following factors: (1) seriousness of the event, (2) frequency of the reporting, or (3) strength of causal connection to the drug.

There have been rare spontaneous reports of myocardial hypertrophy associated with clinically manifested ventricular dysfunction in patients receiving Prograf therapy (see PRECAUTIONS- Myocardial Hypertrophy).

Other events include:

Cardiovascular

Atrial fibrillation, atrial flutter, cardiac arrhythmia, cardiac arrest, electrocardiogram T wave abnormal, flushing, myocardial infarction, myocardial ischaemia, pericardial effusion, QT prolongation, Torsade de Pointes, venous thrombosis deep limb, ventricular extrasystoles, ventricular fibrillation

Gastrointestinal

Bile duct stenosis, colitis, enterocolitis, gastroenteritis, gastrooesophageal reflux disease, hepatic cytolysis, hepatic necrosis, hepatotoxicity, impaired gastric emptying, liver fatty, mouth ulceration, pancreatitis haemorrhagic, pancreatitis necrotizing, stomach ulcer, venoocclusive liver disease

Hemic/Lymphatic

Disseminated intravascular coagulation, neutropenia, pancytopenia, thrombocytopenic purpura, thrombotic thrombocytopenic purpura

Metabolic/Nutritional

Glycosuria, increased amylase including pancreatitis, weight decreased

Miscellaneous

Feeling hot and cold, feeling jittery, hot flushes, multi-organ failure, primary graft dysfunction

Nervous System

Carpal tunnel syndrome, cerebral infarction, hemiparesis, leukoencephalopathy, mental disorder, mutism, posterior reversible encephalopathy syndrome (PRES), progressive multifocal leukoencephalopathy (PML), quadriplegia, speech disorder, syncope

Respiratory

Acute respiratory distress syndrome, interstitial lung disease, lung infiltration, respiratory distress, respiratory failure

Skin

Stevens-Johnson syndrome, toxic epidermal necrolysis

Special Senses

Blindness, blindness cortical, hearing loss including deafness, photophobia

Urogenital

Acute renal failure, cystitis haemorrhagic, hemolytic-uremic syndrome, micturition disorder.

OVERDOSAGE

Limited overdosage experience is available. Acute overdosages of up to 30 times the intended dose have been reported. Almost all cases have been asymptomatic and all patients recovered with no sequelae. Occasionally, acute overdosage has been followed by adverse reactions consistent with those listed in the ADVERSE REACTIONS section except in one case where transient urticaria and lethargy were observed. Based on the poor aqueous solubility and extensive erythrocyte and plasma protein binding, it is anticipated that tacrolimus is not dialyzable to any significant extent; there is no experience with charcoal hemoperfusion. The oral use of activated charcoal has been reported in treating acute overdoses, but experience has not been sufficient to warrant recommending its use. General supportive measures and treatment of specific symptoms should be followed in all cases of overdosage.

In acute oral and IV toxicity studies, mortalities were seen at or above the following doses: in adult rats, 52X the recommended human oral dose; in immature rats, 16X the recommended oral dose; and in adult rats, 16X the recommended human IV dose (all based on body surface area corrections).

DOSAGE AND ADMINISTRATION

Prograf injection (tacrolimus injection)

For IV Infusion Only

NOTE: Anaphylactic reactions have occurred with injectables containing castor oil derivatives. See WARNINGS.

In patients unable to take oral Prograf capsules, therapy may be initiated with Prograf injection. The initial dose of Prograf should be administered no sooner than 6 hours after transplantation. The recommended starting dose of Prograf injection is 0.01 mg/kg/day (heart) or 0.03-0.05 mg/kg/day (liver, kidney) as a continuous IV infusion. Adult patients should receive doses at the lower end of the dosing range. Concomitant adrenal corticosteroid therapy is recommended early post-transplantation. Continuous IV infusion of Prograf injection should be continued only until the patient can tolerate oral administration of Prograf capsules.

Preparation for Administration/Stability

Prograf injection must be diluted with 0.9% Sodium Chloride Injection or 5% Dextrose Injection to a concentration between 0.004 mg/mL and 0.02 mg/mL prior to use. Diluted infusion solution should be stored in glass or polyethylene containers and should be discarded after 24 hours. The diluted infusion solution should not be stored in a PVC container due to decreased stability and the potential for extraction of phthalates. In situations where more dilute solutions are utilized (e.g., pediatric dosing, etc.), PVC-free tubing should likewise be used to minimize the potential for significant drug adsorption onto the tubing. Parenteral drug products should be inspected visually for particulate matter and discoloration prior to administration, whenever solution and container permit. Due to the chemical instability of tacrolimus in alkaline media, Prograf injection should not be mixed or co-infused with solutions of pH 9 or greater (e.g., ganciclovir or acyclovir).

Prograf capsules (tacrolimus capsules)

Summary of Initial Oral Dosage Recommendations and Observed Whole Blood Trough Concentrations
Patient Population | Recommended Initial; Oral Dosage [Note : two divided doses, q12h] | Observed Whole Blood Trough Concentrations
Adult kidney transplant patients; In combination with azathioprine; In combination with MMF/IL-2 receptor; antagonist [In a second smaller study, the initial dose of tacrolimus was 0.15-0.2 mg/kg/day and observed tacrolimus concentrations were 6-16 ng/mL during month 1-3 and 5-12 ng/mL during month 4-12 (see CLINICAL STUDIES).] | 0.2 mg/kg/day; 0.1 mg/kg/day | month 1-3: 7-20 ng/mL; month 4-12: 5-15 ng/mL; month 1-12: 4-11 ng/mL
Adult liver transplant patients | 0.10-0.15 mg/kg/day | month 1-12: 5-20 ng/mL
Pediatric liver transplant patients | 0.15-0.20 mg/kg/day | month 1-12: 5-20 ng/mL
Adult heart transplant patients | 0.075 mg/kg/day | month 1-3: 10-20 ng/mL; month ≥4: 5-15 ng/mL

Liver Transplantation

It is recommended that patients initiate oral therapy with Prograf capsules if possible. If IV therapy is necessary, conversion from IV to oral Prograf is recommended as soon as oral therapy can be tolerated. This usually occurs within 2-3 days. The initial dose of Prograf should be administered no sooner than 6 hours after transplantation. In a patient receiving an IV infusion, the first dose of oral therapy should be given 8-12 hours after discontinuing the IV infusion. The recommended starting oral dose of Prograf capsules is 0.10 to 0.15 mg/kg/day administered in two divided daily doses every 12 hours. Co-administered grapefruit juice has been reported to increase tacrolimus blood trough concentrations in liver transplant patients. (See Drugs that May Alter Tacrolimus Concentrations).

Dosing should be titrated based on clinical assessments of rejection and tolerability. Lower Prograf dosages may be sufficient as maintenance therapy. Adjunct therapy with adrenal corticosteroids is recommended early post-transplant.

Dosage and typical tacrolimus whole blood trough concentrations are shown in the table above; blood concentration details are described in Blood Concentration Monitoring: Liver Transplantation below.

Kidney Transplantation

The recommended starting oral dose of Prograf (administered every 12 hours in two divided doses) is 0.2 mg/kg/day when used in combination with azathioprine or 0.1 mg/kg/day when used in combination with MMF and IL-2 receptor antagonist (see CLINICAL STUDIES). The initial dose of Prograf may be administered within 24 hours of transplantation, but should be delayed until renal function has recovered (as indicated for example by a serum creatinine ≤ 4 mg/dL). Black patients may require higher doses to achieve comparable blood concentrations. Dosage and typical tacrolimus whole blood trough concentrations are shown in the table above; blood concentration details are described in Blood Concentration Monitoring: Kidney Transplantation below.

The data in kidney transplant patients indicate that the Black patients required a higher dose to attain comparable trough concentrations compared to Caucasian patients.

Time After Transplant | Caucasian; n=114 |  | Black; n=56
Time After Transplant | Dose; (mg/kg) | Trough Concentrations; (ng/mL) | Dose; (mg/kg) | Trough Concentrations (ng/mL)
Day 7 | 0.18 | 12.0 | 0.23 | 10.9
Month 1 | 0.17 | 12.8 | 0.26 | 12.9
Month 6 | 0.14 | 11.8 | 0.24 | 11.5
Month 12 | 0.13 | 10.1 | 0.19 | 11.0

Heart Transplantation

The recommended starting oral dose of Prograf is 0.075 mg/kg/day administered every 12 hours in two divided doses. If possible, initiating oral therapy with Prograf capsules is recommended. If IV therapy is necessary, conversion from IV to oral Prograf is recommended as soon as oral therapy can be tolerated. This usually occurs within 2-3 days. The initial dose of Prograf should be administered no sooner than 6 hours after transplantation. In a patient receiving an IV infusion, the first dose of oral therapy should be given 8-12 hours after discontinuing the IV infusion.

Dosing should be titrated based on clinical assessments of rejection and tolerability. Lower Prograf dosages may be sufficient as maintenance therapy. Adjunct therapy with adrenal corticosteroids is recommended early post transplant.

Dosage and typical tacrolimus whole blood trough concentrations are shown in the table above; blood concentration details are described in Blood Concentration Monitoring: Heart Transplantationbelow.

Pediatric Patients

Pediatric liver transplantation patients without pre-existing renal or hepatic dysfunction have required and tolerated higher doses than adults to achieve similar blood concentrations. Therefore, it is recommended that therapy be initiated in pediatric patients at a starting IV dose of 0.03-0.05 mg/kg/day and a starting oral dose of 0.15-0.20 mg/kg/day. Dose adjustments may be required. Experience in pediatric kidney and heart transplantation patients is limited.

Patients with Hepatic or Renal Dysfunction

Due to the reduced clearance and prolonged half-life, patients with severe hepatic impairment (Pugh ≥ 10) may require lower doses of Prograf. Close monitoring of blood concentrations is warranted.

Due to the potential for nephrotoxicity, patients with renal or hepatic impairment should receive doses at the lowest value of the recommended IV and oral dosing ranges. Further reductions in dose below these ranges may be required. Prograf therapy usually should be delayed up to 48 hours or longer in patients with post-operative oliguria.

Conversion from One Immunosuppressive Regimen to Another

Prograf should not be used simultaneously with cyclosporine. Prograf or cyclosporine should be discontinued at least 24 hours before initiating the other. In the presence of elevated Prograf or cyclosporine concentrations, dosing with the other drug usually should be further delayed.

Blood Concentration Monitoring

Monitoring of tacrolimus blood concentrations in conjunction with other laboratory and clinical parameters is considered an essential aid to patient management for the evaluation of rejection, toxicity, dose adjustments and compliance. Factors influencing frequency of monitoring include but are not limited to hepatic or renal dysfunction, the addition or discontinuation of potentially interacting drugs and the posttransplant time. Blood concentration monitoring is not a replacement for renal and liver function monitoring and tissue biopsies.

Two methods have been used for the assay of tacrolimus, a microparticle enzyme immunoassay (MEIA) and ELISA. Both methods have the same monoclonal antibody for tacrolimus. Comparison of the concentrations in published literature to patient concentrations using the current assays must be made with detailed knowledge of the assay methods and biological matrices employed. Whole blood is the matrix of choice and specimens should be collected into tubes containing ethylene diamine tetraacetic acid (EDTA) anti-coagulant. Heparin anti-coagulation is not recommended because of the tendency to form clots on storage. Samples which are not analyzed immediately should be stored at room temperature or in a refrigerator and assayed within 7 days; if samples are to be kept longer they should be deep frozen at -20° C for up to 12 months.

Liver Transplantation

Although there is a lack of direct correlation between tacrolimus concentrations and drug efficacy, data from Phase II and III studies of liver transplant patients have shown an increasing incidence of adverse events with increasing trough blood concentrations. Most patients are stable when trough whole blood concentrations are maintained between 5 to 20 ng/mL. Long-term post-transplant patients often are maintained at the low end of this target range.

Data from the U.S. clinical trial show that tacrolimus whole blood concentrations, as measured by ELISA, were most variable during the first week post-transplantation. After this early period, the median trough blood concentrations, measured at intervals from the second week to one year post-transplantation, ranged from 9.8 ng/mL to 19.4 ng/mL.

Therapeutic Drug Monitoring, 1995, Volume 17, Number 6 contains a consensus document and several position papers regarding the therapeutic monitoring of tacrolimus from the 1995 International Consensus Conference on Immunosuppressive Drugs. Refer to these manuscripts for further discussions of tacrolimus monitoring.

Kidney Transplantation

Data from a Phase 3 study of Prograf in conjunction with azathioprine indicate that trough concentrations of tacrolimus in whole blood, as measured by IMx® were most variable during the first week of dosing. During the first three months of that trial, 80% of the patients maintained trough concentrations between 7-20 ng/mL, and then between 5-15 ng/mL, through 1 year.

In a separate clinical trial of Prograf in conjunction with MMF and daclizumab, approximately 80% of patients maintained tacrolimus whole blood concentrations between 4-11 ng/mL through 1 year post-transplant.

In another clinical trial of Prograf in conjunction with MMF and basiliximab, approximately 80% of patients maintained tacrolimus whole trough blood concentrations between 6-16 ng/mL during month 1-3 and, then, between 5-12 ng/mL from month 4 through 1 year.

The relative risks of toxicity and efficacy failure are related to tacrolimus whole blood trough concentrations. Therefore, monitoring of whole blood trough concentrations is recommended to assist in the clinical evaluation of toxicity and efficacy failure.

Heart Transplantation

Data from a European Phase 3 study indicate that trough concentrations of tacrolimus in whole blood, as measured by IMx® were most variable during the first week of dosing. From 1 week to 3 months post transplant, approximately 80% of patients maintained trough concentrations between 8-20 ng/mL and, from 3 months through 18 months post transplant, approximately 80% of patients maintained trough concentrations between 6-18 ng/mL.

The relative risk of toxicity; for example, nephrotoxicity and post-transplant diabetes mellitus, is increased with higher trough concentrations. Therefore, monitoring of whole blood trough concentrations is recommended to assist in the clinical evaluation of toxicity.

HOW SUPPLIED

Prograf capsules (tacrolimus capsules)
strength | 1 mg; (containing the equivalent of 1 mg anhydrous tacrolimus)
shape/color | oblong/white
branding on capsule cap/body | f; 617
100 count bottle | NDC 21695-170-00

Made in Japan

Store and Dispense

Store at 25°C (77°F); excursions permitted to 15°C-30°C (59°F-86°F).

Prograf injection (tacrolimus injection)

(for IV infusion only)

NDC 0469-3016-01 Product Code 301601

5 mg/mL (equivalent of 5 mg of anhydrous tacrolimus per mL) supplied as a sterile solution in a 1 mL ampule, in boxes of 10 ampules

Made in Ireland

Store and Dispense

Store between 5°C and 25°C (41°F and 77°F).

Rx only

Marketed by:

Astellas Pharma US, Inc.

Deerfield, IL 60015-2548

Revised: August 2009

09H011PRG-CPI

Repackaged by:

Rebel Distributors Corp

Thousand Oaks, CA 91320

REFERENCE

1.CDC: Recommendations of the Advisory Committee on Immunization Practices: Use of vaccines and immune globulins in persons with altered immunocompetence. MMWR 1993;42(RR-4):1-18.